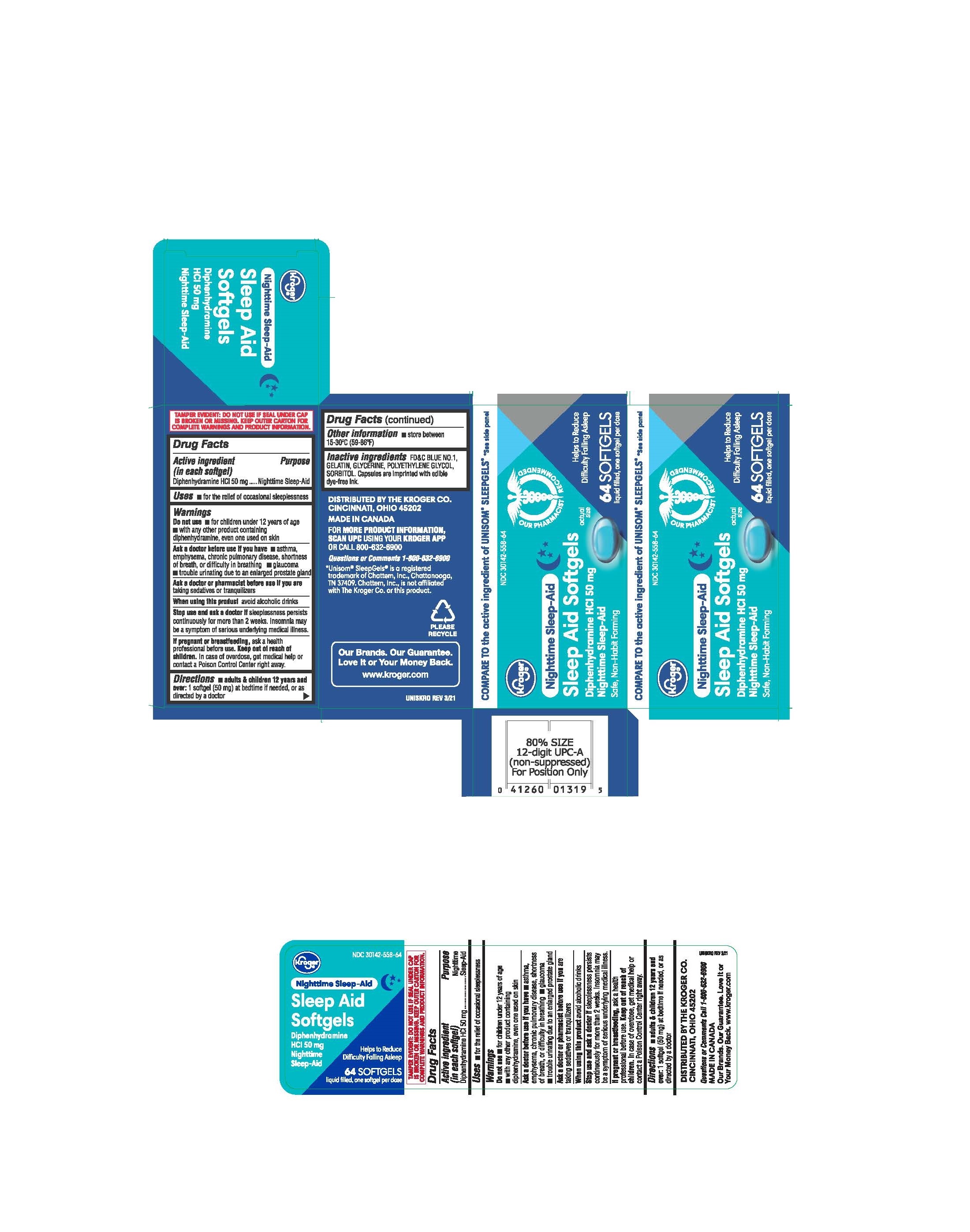 DRUG LABEL: Kroger Nighttime Sleep-Aid
NDC: 30142-558 | Form: CAPSULE, LIQUID FILLED
Manufacturer: THE KROGER CO
Category: otc | Type: HUMAN OTC DRUG LABEL
Date: 20241218

ACTIVE INGREDIENTS: DIPHENHYDRAMINE HYDROCHLORIDE 50 mg/1 1
INACTIVE INGREDIENTS: FD&C BLUE NO. 1; GELATIN; GLYCERIN; POLYETHYLENE GLYCOL, UNSPECIFIED; SORBITOL

Active ingredient

(in each softgel)

Diphenhydramine HCI 50 mg

Purpose

Nighttime sleep-aid

Use

- for relief of occasional sleeplessness

Warnings

Do not use

- for children under 12 years of age
- with any other product containing diphenhydramine, even one used on skin

Ask a doctor before use if you have

- a breathing problem such as emphysema or chronic bronchitis
- glaucoma
- trouble urinating due to an enlarged prostate gland

Ask a doctor or pharmacist before use if you are

taking sedatives or tranquilizers

When using this product

avoid alcoholic drinks

Stop use and ask a doctor if

sleeplessness persist continuously for more than 2 weeks. Insomnia may be a symptom of serious underlying medical illness.

If pregnant or breast-feeding,

ask a health professional before use.

Keep out of reach of children.

In case of overdose, get medical help or contact a Poison Control Center right away.

Directions

- adults and children 12 years of age and over: 1 softgel (50 mg) at bedtime if needed, or as directed by a doctor

Inactive ingredients

FD&C Blue No. 1, Gelatin, Glycerine, Polyethylene Glycol, Sorbitol.

PRINCIPAL DISPLAY PANEL

DISTRIBUTED BY THE KROGER CO.

CINCINNATI, OHIO 45202

MADE IN CANADA

FOR MORE PRODUCT INFORMATION,

SCAN UPC USING YOUR KROGER APP

OR CALL 800-632-6900

Questions or Comments 1-800-632-6900

UNISKRO REV 3/21